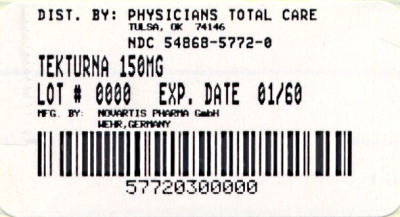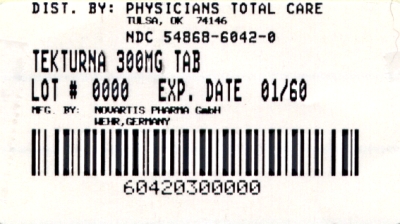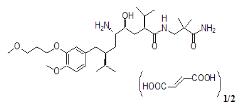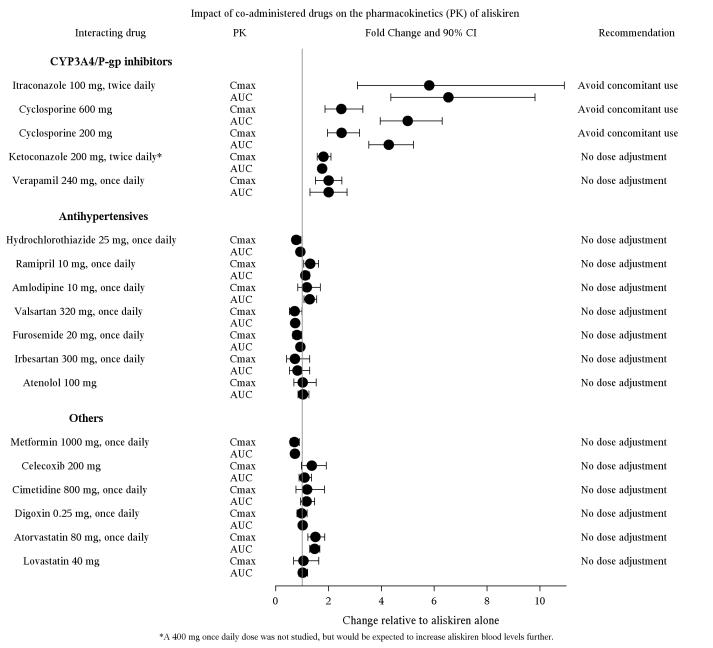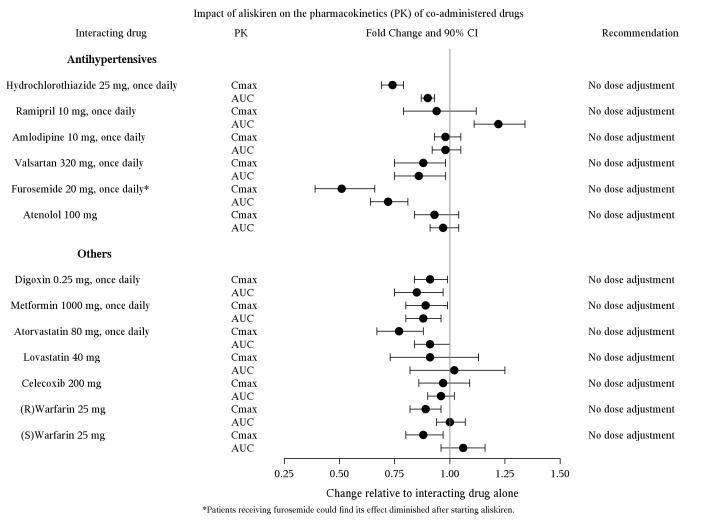 DRUG LABEL: Tekturna
NDC: 54868-5772 | Form: TABLET, FILM COATED
Manufacturer: Physicians Total Care, Inc.
Category: prescription | Type: HUMAN PRESCRIPTION DRUG LABEL
Date: 20120113

ACTIVE INGREDIENTS: ALISKIREN HEMIFUMARATE 150 mg/1 1
INACTIVE INGREDIENTS: SILICON DIOXIDE, COLLOIDAL; CROSPOVIDONE; HYPROMELLOSES; FERRIC OXIDE RED; MAGNESIUM STEARATE; CELLULOSE, MICROCRYSTALLINE; POLYETHYLENE GLYCOL; TALC; TITANIUM DIOXIDE; FERROSOFERRIC OXIDE

HIGHLIGHTS OF PRESCRIBING INFORMATION

These highlights do not include all the information needed to use TEKTURNA® safely and effectively. See full prescribing information for TEKTURNA®.
Tekturna® (aliskiren) tablets, for oral use
Initial U.S. Approval: 2007

RECENT MAJOR CHANGES

Indications and Usage: Benefits of lowering blood pressure (1.1) 10/2011

Warnings and Precautions, Cyclosporine or Itraconazole (5.7) 02/2011

WARNING: AVOID USE IN PREGNANCY

See full prescribing information for complete boxed warning

When pregnancy is detected, discontinue Tekturna as soon as possible. Drugs that act directly on the renin-angiotensin system can cause injury and death to the developing fetus. (5.1)

1 INDICATIONS AND USAGE

Tekturna is a renin inhibitor (RI) indicated for:

- The treatment of hypertension, to lower blood pressure (1.1)

Lowering blood pressure reduces the risk of fatal and nonfatal cardiovascular events, primarily strokes and myocardial infarctions.

2 DOSAGE AND ADMINISTRATION

- Majority of effect of given dose substantially attained in 2 weeks (2.1)
- May be administered with other anti-hypertensive agents (2.2)
- Additive effects with angiotensin-converting enzyme inihibitors (ACEI) at maximal doses have not been studied (2.2)
- Starting dose: 150 mg once daily with a routine pattern with regard to meals. If blood pressure remains uncontrolled titrate up to 300 mg daily (2.1, 2.3)
- No initial dosage adjustment required in the elderly, in patients with mild to severe renal or hepatic impairment. (2.4, 12.3)

3 DOSAGE FORMS AND STRENGTHS

Tablets: 150 mg, 300 mg (3)

4 CONTRAINDICATIONS

None (4)

5 WARNINGS AND PRECAUTIONS

- Avoid neonatal/fetal exposure (5.1)
- Head and neck angioedema. Discontinue use of Tekturna and monitor until signs and symptoms resolve (5.2)
- Hypotension in volume and/or salt depleted patients: Correct imbalances before initiating therapy with Tekturna (5.3)
- Patients with severe renal dysfunction: Consider periodic determinations of serum electrolytes to detect possible electrolyte imbalances (5.4)
- Hyperkalemia: Caution should be exercised when co-administered with ACEI, potassium-sparing diuretics, potassium supplements or other potassium containing salt substitutes (5.5)

6 ADVERSE REACTIONS

Most common adverse reaction: diarrhea (incidence 2.3%) (6.1)

To report SUSPECTED ADVERSE REACTIONS, contact Novartis Pharmaceuticals Corporation at 1-888-669-6682 or FDA at 1-800-FDA-1088 or www.fda.gov/medwatch.

7 DRUG INTERACTIONS

- Cyclosporine: Avoid concomitant use (7, 12.3)
- Itraconazole: Avoid concomitant use (7, 12.3)

8 USE IN SPECIFIC POPULATIONS

Nursing Mothers: Adverse reactions may occur in nursing infants (8.3)

FULL PRESCRIBING INFORMATION

WARNING: AVOID USE IN PREGNANCY

When pregnancy is detected, discontinue Tekturna as soon as possible. Drugs that act directly on the renin-angiotensin system can cause injury and death to the developing fetus. [See Warnings and Precautions (5.1)]

1 INDICATIONS AND USAGE

1.1 Hypertension

Tekturna is indicated for the treatment of hypertension, to lower blood pressure. Lowering blood pressure reduces the risk of fatal and nonfatal cardiovascular events, primarily strokes and myocardial infarctions. These benefits have been seen in controlled trials of antihypertensive drugs from a wide variety of pharmacologic classes. There are no controlled trials demonstrating risk reduction with Tekturna.

Control of high blood pressure should be part of comprehensive cardiovascular risk management, including, as appropriate, lipid control, diabetes management, antithrombotic therapy, smoking cessation, exercise, and limited sodium intake. Many patients will require more than one drug to achieve blood pressure goals. For specific advice on goals and management, see published guidelines, such as those of the National High Blood Pressure Education Program’s Joint National Committee on Prevention, Detection, Evaluation, and Treatment of High Blood Pressure (JNC).

Numerous antihypertensive drugs, from a variety of pharmacologic classes and with different mechanisms of action, have been shown in randomized controlled trials to reduce cardiovascular morbidity and mortality, and it can be concluded that it is blood pressure reduction, and not some other pharmacologic property of the drugs, that is largely responsible for those benefits. The largest and most consistent cardiovascular outcome benefit has been a reduction in the risk of stroke, but reductions in myocardial infarction and cardiovascular mortality also have been seen regularly.

Elevated systolic or diastolic pressure causes increased cardiovascular risk, and the absolute risk increase per mmHg is greater at higher blood pressures, so that even modest reductions of severe hypertension can provide substantial benefit. Relative risk reduction from blood pressure reduction is similar across populations with varying absolute risk, so the absolute benefit is greater in patients who are at higher risk independent of their hypertension (for example, patients with diabetes or hyperlipidemia), and such patients would be expected to benefit from more aggressive treatment to a lower blood pressure goal.

Some antihypertensive drugs have smaller blood pressure effects (as monotherapy) in black patients, and many antihypertensive drugs have additional approved indications and effects (e.g., on angina, heart failure, or diabetic kidney disease). These considerations may guide selection of therapy.

Tekturna may be used alone or in combination with other antihypertensive agents. Use with maximal doses of ACE inhibitors has not been adequately studied.

2 DOSAGE AND ADMINISTRATION

2.1 Hypertension

The usual recommended starting dose of Tekturna is 150 mg once daily. In patients whose blood pressure is not adequately controlled, the daily dose may be increased to 300 mg. Doses above 300 mg did not give an increased blood pressure response but resulted in an increased rate of diarrhea. The antihypertensive effect of a given dose is substantially attained (85-90%) by 2 weeks.

2.2 Use with Other Antihypertensives

Tekturna may be administered with other antihypertensive agents. Most exposure to date is with diuretics, an angiotensin receptor blocker (valsartan) or a calcium channel blocker (amlodipine). Aliskiren used together with these drugs has a greater effect at their maximum recommended doses than either drug alone. It is not known whether additive effects are present when Tekturna is used with angiotensin-converting enzyme inhibitors (ACEI) or beta blockers (BB).

2.3 Relationship to Meals

Patients should establish a routine pattern for taking Tekturna with regard to meals. High fat meals decrease absorption substantially [see Clinical Pharmacology (12.3)].

2.4 Dosing in Special Populations

No adjustment of the starting dose is required in elderly patients, patients with mild-to-severe renal impairment or mild-to-severe hepatic insufficiency. However, clinical experience in patients with severe renal impairment is limited [See Clinical Pharmacology (12.3) and Warnings and Precautions (5.4)].

3 DOSAGE FORMS AND STRENGTHS

150 mg light pink biconvex round tablet, imprinted NVR/IL (Side 1/Side 2)

300 mg light red biconvex ovaloid round tablet, imprinted NVR/IU (Side 1/Side 2)

4 CONTRAINDICATIONS

None.

5 WARNINGS AND PRECAUTIONS

5.1 Fetal/neonatal morbidity and mortality

Drugs that act directly on the renin-angiotensin system can cause fetal and neonatal morbidity and death when administered to pregnant women. If this drug is used during pregnancy, or if the patient becomes pregnant while taking this drug, the patient should be apprised of the potential hazard to the fetus [see Use in Specific Populations (8.1)]. In several dozen published cases, ACE inhibitor use during the second and third trimesters of pregnancy was associated with fetal and neonatal injury, including hypotension, neonatal skull hypoplasia, anuria, reversible or irreversible renal failure, and death. In addition, first trimester use of ACE inhibitors has been associated with birth defects in retrospective data.

5.2 Head and Neck Angioedema

Angioedema of the face, extremities, lips, tongue, glottis and/or larynx has been reported in patients treated with Tekturna and has necessitated hospitalization and intubation. This may occur at any time during treatment and has occurred in patients with and without a history of angioedema with ACE inhibitors or angiotensin receptor antagonists. If angioedema involves the throat, tongue, glottis or larynx, or if the patient has a history of upper respiratory surgery, airway obstruction may occur and be fatal. Patients who experience these effects, even without respiratory distress, require prolonged observation since treatment with antihistamines and corticosteroids may not be sufficient to prevent respiratory involvement. Prompt administration of subcutaneous epinephrine solution 1:1000 (0.3 to 0.5 ml) and measures to ensure a patent airway may be necessary.

Discontinue Tekturna immediately in patients who develop angioedema, and do not readminister.

5.3 Hypotension

An excessive fall in blood pressure was rarely seen (0.1%) in patients with uncomplicated hypertension treated with Tekturna alone in controlled trials and in <1% during combination therapy with other antihypertensive agents. In patients with an activated renin-angiotensin system, such as volume- and/or salt-depleted patients (e.g., those receiving high doses of diuretics), symptomatic hypotension may occur after initiation of treatment with Tekturna. This condition should be corrected prior to administration of Tekturna, or the treatment should start under close medical supervision.

If an excessive fall in blood pressure occurs, the patient should be placed in the supine position and, if necessary, given an intravenous infusion of normal saline. A transient hypotensive response is not a contraindication to further treatment, which usually can be continued without difficulty once the blood pressure has stabilized.

5.4 Impaired Renal Function

Patients with greater than moderate renal dysfunction (creatinine 1.7 mg/dL for women and 2.0 mg/dL for men and/or estimated GFR <30 ml/min), a history of dialysis, nephrotic syndrome, or renovascular hypertension were excluded from clinical trials of Tekturna in hypertension. Consider periodic determinations of serum electrolytes to detect possible electrolyte imbalances particularly in patients with severe renal impairment.

5.5 Hyperkalemia

Increases in serum potassium >5.5 mEq/L were infrequent with Tekturna alone (0.9% compared to 0.6% with placebo). However, when used in combination with an ACE inhibitor in a diabetic population, increases in serum potassium were more frequent (5.5%). Routine monitoring of electrolytes and renal function is indicated in this population. Concomitant use of Tekturna with potassium-sparing diuretics, potassium supplements, salt substitutes containing potassium, or other drugs that increase potassium levels may lead to increases in serum potassium.

5.6 Renal Artery Stenosis

No data are available on the use of Tekturna in patients with unilateral or bilateral renal artery stenosis or stenosis of the artery to a solitary kidney.

5.7 Cyclosporine or Itraconazole

When aliskiren was given with cyclosporine or itraconazole, the blood concentrations of aliskiren were significantly increased. Avoid concomitant use of aliskiren with cyclosporine or itraconazole [see Drug Interactions (7)].

6 ADVERSE REACTIONS

6.1 Clinical Trials Experience

Because clinical trials are conducted under widely varying conditions, adverse reaction rates observed in the clinical trials of a drug cannot be directly compared to rates in clinical trials of another drug and may not reflect the rates observed in practice.

Data described below reflect the evaluation of the safety of Tekturna in more than 6,460 patients, including over 1,740 treated for longer than 6 months, and more than 1,250 patients for longer than 1 year. In placebo controlled clinical trials, discontinuation of therapy due to a clinical adverse event, including uncontrolled hypertension occurred in 2.2% of patients treated with Tekturna vs. 3.5% of patients given placebo.

Angioedema: Two cases of angioedema with respiratory symptoms were reported with Tekturna use in the clinical studies. Two other cases of periorbital edema without respiratory symptoms were reported as possible angioedema and resulted in discontinuation. The rate of these angioedema cases in the completed studies was 0.06%. In addition, 26 other cases of edema involving the face, hands, or whole body were reported with Tekturna use including 4 leading to discontinuation. In the placebo controlled studies, however, the incidence of edema involved the face, hands or whole body was 0.4% with Tekturna compared with 0.5% with placebo. In a long term active control study with Tekturna and HCTZ arms, the incidence of edema involving the face, hand or whole body was 0.4% in both treatment arms [see Warnings and Precautions (5.2)].

Gastrointestinal: Tekturna produces dose-related gastrointestinal (GI) adverse reactions. Diarrhea was reported by 2.3% of patients at 300 mg, compared to 1.2% in placebo patients. In women and the elderly (age ≥ 65) increases in diarrhea rates were evident starting at a dose of 150 mg daily, with rates for these subgroups at 150 mg comparable to those seen at 300 mg for men or younger patients (all rates about 2.0-2.3%). Other GI symptoms included abdominal pain, dyspepsia, and gastroesophageal reflux, although increased rates for abdominal pain and dyspepsia were distinguished from placebo only at 600 mg daily. Diarrhea and other GI symptoms were typically mild and rarely led to discontinuation.

Cough: Tekturna was associated with a slight increase in cough in the placebo-controlled studies (1.1% for any Tekturna use vs. 0.6% for placebo). In active-controlled trials with ACE inhibitor (ramipril, lisinopril) arms the rates of cough for the Tekturna arms were about one-third to one-half the rates in the ACE inhibitor arms.

Seizures: Single episodes of tonic-clonic seizures with loss of consciousness were reported in two patients treated with Tekturna in the clinical trials. One of these patients did have predisposing causes for seizures and had a negative electroencephalogram (EEG) and cerebral imaging following the seizures (for the other patient EEG and imaging results were not reported). Tekturna was discontinued and there was no re-challenge.

The following adverse events occurred in placebo-controlled clinical trials at an incidence of more than 1% of patients treated with Tekturna, but also occurred at about the same or greater incidence in patients receiving placebo: headache, nasopharyngitis, dizziness, fatigue, upper respiratory tract infection, back pain and cough.

Other adverse effects with increased rates for Tekturna compared to placebo included rash (1% vs. 0.3%), elevated uric acid (0.4% vs. 0.1%), gout (0.2% vs. 0.1%) and renal stones (0.2% vs. 0%).

Aliskiren’s effect on ECG intervals was studied in a randomized, double-blind, placebo and active-controlled (moxifloxacin), 7-day repeat dosing study with Holter-monitoring and 12 lead ECGs throughout the interdosing interval. No effect of aliskiren on QT interval was seen.

Clinical Laboratory Findings

In controlled clinical trials, clinically relevant changes in standard laboratory parameters were rarely associated with the administration of Tekturna. In multiple-dose studies in hypertensive patients, Tekturna had no clinically important effects on total cholesterol, HDL, fasting triglycerides, fasting glucose, or uric acid.

Blood Urea Nitrogen, Creatinine: Minor increases in blood urea nitrogen (BUN) or serum creatinine were observed in less than 7% of patients with essential hypertension treated with Tekturna alone vs. 6% on placebo.

Hemoglobin and Hematocrit: Small decreases in hemoglobin and hematocrit (mean decreases of approximately 0.08 g/dL and 0.16 volume percent, respectively, for all aliskiren monotherapy) were observed. The decreases were dose-related and were 0.24 g/dL and 0.79 volume percent for 600 mg daily. This effect is also seen with other agents acting on the renin angiotensin system, such as angiotensin inhibitors and angiotensin receptor blockers and may be mediated by reduction of angiotensin II which stimulates erythropoetin production via the AT1 receptor. These decreases led to slight increases in rates of anemia with aliskiren compared to placebo were observed (0.1% for any aliskiren use, 0.3% for aliskiren 600 mg daily, vs 0% for placebo). No patients discontinued therapy due to anemia.

Serum Potassium: Increases in serum potassium >5.5 mEq/L were infrequent in patients with essential hypertension treated with Tekturna alone (0.9% compared to 0.6% with placebo). However, when used in combination with an angiotensin-converting enzyme inhibitor (ACEI) in a diabetic population increases in serum potassium were more frequent (5.5%) and routine monitoring of electrolytes and renal function is indicated in this population.

Serum Uric Acid: Aliskiren monotherapy produced small median increases in serum uric acid levels (about 6 μmol/L) while HCTZ produced larger increases (about 30 μmol/L). The combination of aliskiren with HCTZ appears to be additive (about 40 μmol/L increase). The increases in uric acid appear to lead to slight increases in uric acid-related AEs: elevated uric acid (0.4% vs 0.1%), gout (0.2% vs. 0.1%), and renal stones (0.2% vs 0%).

Creatine Kinase: Increases in creatine kinase of >300% were recorded in about 1% of aliskiren monotherapy patients vs. 0.5% of placebo patients. Five cases of creatine kinase rises, three leading to discontinuation and one diagnosed as subclinical rhabdomyolysis, and another as myositis, were reported as adverse events with aliskiren use in the clinical trials. No cases were associated with renal dysfunction.

6.2 Postmarketing Experience

The following adverse reactions have been reported in aliskiren post-marketing experience. Because these reactions are reported voluntarily from a population of uncertain size, it is not always possible to estimate their frequency or establish a causal relationship to drug exposure.

Hypersensitivity: angioedema requiring airway management and hospitalization

Peripheral edema

Blood creatinine increased

7 DRUG INTERACTIONS

Cyclosporine:Avoid co-administration of cyclosporine with aliskiren.

Itraconazole: Avoid co-administration of itraconazole with aliskiren.

[See Clinical Pharmacology (12.3).]

8 USE IN SPECIFIC POPULATIONS

8.1 Pregnancy

Pregnancy Categories C (first trimester) and D (second and third trimesters) [see Warnings and Precautions (5.1)].

There is no clinical experience with the use of Tekturna in pregnant women.

Drugs that act directly on the renin-angiotensin system can cause fetal and neonatal morbidity and death when administered to pregnant women. Several dozen cases have been reported in the world literature in patients who were taking angiotensin-converting enzyme inhibitors. When pregnancy is detected, Tekturna should be discontinued as soon as possible. The use of drugs that act directly on the renin-angiotensin system during the second and third trimesters of pregnancy has been associated with fetal and neonatal injury, including hypotension, neonatal skull hypoplasia, anuria, reversible or irreversible renal failure, and death. Oligohydramnios has also been reported, presumably resulting from decreased fetal renal function; oligohydramnios in this setting has been associated with fetal contractures, craniofacial deformation, and hypoplastic lung development. Prematurity, intrauterine growth retardation, and patent ductus arteriosus have also been reported, although it is not clear whether these occurrences were due to exposure to the drug.

In addition, first trimester use of ACE inhibitors, a specific class of drugs acting on the renin-angiotensin system, has been associated with a potential risk of birth defects in retrospective data. Healthcare professionals that prescribe drugs acting directly on the renin-angiotensin system should counsel women of childbearing potential about the potential risks of these agents during pregnancy. Rarely (probably less often than once in every thousand pregnancies), no alternative to a drug acting on the renin-angiotensin system will be found. In these rare cases, the mothers should be apprised of the potential hazards to their fetuses and serial ultrasound examination should be performed to assess the intra-amniotic environment. If oligohydramnios is observed, Tekturna should be discontinued unless it is considered life-saving for the mother. Contraction stress testing (CST), a nonstress test (NST) or biophysical profiling (BPP) may be appropriate, depending upon the week of pregnancy. Patients and physicians should be aware; however that oligohydraminos may not appear until after the fetus has sustained irreversible injury.

Infants with histories of in-utero exposure to a renin inhibitor should be closely observed for hypotension, oliguria, and hyperkalemia. If oliguria occurs, attention should be directed toward support of blood pressure and renal perfusion. Exchange transfusion or dialysis may be required as means of reversing hypotension and/or substituting for disordered renal function. [See Nonclinical Toxicology (13).]

8.3 Nursing Mothers

It is not known whether aliskiren is excreted in human breast milk. Aliskiren was secreted in the milk of lactating rats. Because of the potential for adverse effects on the nursing infant, a decision should be made whether to discontinue nursing or discontinue the drug, taking into account the importance of the drug to the mother.

8.4 Pediatric Use

Safety and effectiveness of aliskiren in pediatric patients <18 years have not been established.

8.5 Geriatric Use

Of the total number of patients receiving aliskiren in clinical studies, 1,275 (19%) were 65 years or older and 231 (3.4%) were 75 years or older. No overall differences in safety or effectiveness were observed between these subjects and younger subjects. Other reported clinical experience has not identified differences in responses between the elderly and younger patients, but greater sensitivity of some older individuals cannot be ruled out.

10 OVERDOSAGE

Limited data area available related to overdosage in humans. The most likely manifestation of overdosage would be hypotension. If symptomatic hypotension occurs, supportive treatment should be initiated.

11 DESCRIPTION

Tekturna contains aliskiren hemifumarate, a renin inhibitor, that is provided as tablets for oral administration. Aliskiren hemifumarate is chemically described as (2S,4S,5S,7S)-N-(2-carbamoyl-2-methylpropyl)-5-amino-4-hydroxy-2,7-diisopropyl-8-[4-methoxy-3-(3-methoxypropoxy)phenyl]-octanamide hemifumarate and its structural formula is

Molecular formula: C30H53N3O6 • 0.5 C4H4O4

Aliskiren hemifumarate is a white to slightly yellowish crystalline powder with a molecular weight of 609.8 (free base- 551.8). It is soluble in phosphate buffer, n-octanol, and highly soluble in water.

12 CLINICAL PHARMACOLOGY

12.1 Mechanism of Action

Renin is secreted by the kidney in response to decreases in blood volume and renal perfusion. Renin cleaves angiotensinogen to form the inactive decapeptide angiotensin I (Ang I). Ang I is converted to the active octapeptide angiotensin II (Ang II) by angiotensin-converting enzyme (ACE) and non-ACE pathways. Ang II is a powerful vasoconstrictor and leads to the release of catecholamines from the adrenal medulla and prejunctional nerve endings. It also promotes aldosterone secretion and sodium reabsorption. Together, these effects increase blood pressure. Ang II also inhibits renin release, thus providing a negative feedback to the system. This cycle, from renin through angiotensin to aldosterone and its associated negative feedback loop, is known as the renin-angiotensin-aldosterone system (RAAS). Aliskiren is a direct renin inhibitor, decreasing plasma renin activity (PRA) and inhibiting the conversion of angiotensinogen to Ang I. Whether aliskiren affects other RAAS components, e.g., ACE or non-ACE pathways, is not known.

All agents that inhibit the RAAS, including renin inhibitors, suppress the negative feedback loop, leading to a compensatory rise in plasma renin concentration. When this rise occurs during treatment with ACE inhibitors and ARBs, the result is increased levels of PRA. During treatment with aliskiren, however, the effect of increased renin levels is blocked so that PRA, Ang I and Ang II are all reduced, whether aliskiren is used as monotherapy or in combination with other antihypertensive agents.

12.2 Pharmacodynamics

In placebo controlled clinical trials, plasma renin activity (PRA) was decreased in a range of 50- 80%. This reduction in PRA was not dose-related and did not correlate with blood pressure reductions. The clinical implications of the differences in effect on PRA are not known.

12.3 Pharmacokinetics

Aliskiren is poorly absorbed (bioavailability about 2.5%) with an approximate accumulation half life of 24 hours. Steady state blood levels are reached in about 7-8 days.

Absorption and Distribution

Following oral administration, peak plasma concentrations of aliskiren are reached within 1 – 3 hours. When taken with a high fat meal, mean AUC and Cmax of aliskiren are decreased by 71% and 85% respectively. In the clinical trials of aliskiren, it was administered without requiring a fixed relation of administration to meals.

Metabolism and Elimination

About one fourth of the absorbed dose appears in the urine as parent drug. How much of the absorbed dose is metabolized is unknown. Based on the in vitro studies, the major enzyme responsible for aliskiren metabolism appears to be CYP 3A4. Aliskiren does not inhibit the CYP450 isoenzymes (CYP 1A2, 2C8, 2C9, 2C19, 2D6, 2E1, and 3A) or induce CYP 3A4.

Transporters: Pgp (MDR1/Mdr1a/1b) was found to be the major efflux system involved in absorption and disposition of aliskiren in preclinical studies. The potential for drug interactions at the Pgp site will likely depend on the degree of inhibition of this transporter.

Drug interactions

The effect of co-administered drugs on the pharmacokinetics of aliskiren and vice versa, were studied in several single and multiple dose studies. Pharmacokinetic measures indicating the magnitude of these interactions are presented in Figure 1 (impact of co-administered drugs on aliskiren) and Figure 2 (impact of aliskiren on co-administered drugs).

Figure 1: The impact of co-administered drugs on the pharmacokinetics of aliskiren.

Warfarin: There was no clinically significant effect of a single dose of warfarin 25 mg on the pharmacokinetics of aliskiren.

Figure 2: The impact of aliskiren on the pharmacokinetics of co-administered drugs.

Special Populations

Renally Impaired Patients: Aliskiren was evaluated in patients with varying degrees of renal insufficiency. The rate and extent of exposure (AUC and Cmax) of aliskiren in subjects with renal impairment did not show a consistent correlation with the severity of renal impairment. Adjustment of the starting dose is not required in these patients [see Dosage and Administration (2.4)].

Hepatically Impaired Patients: The pharmacokinetics of aliskiren were not significantly affected in patients with mild to severe liver disease. Consequently, adjustment of the starting dose is not required in these patients [see Dosage and Administration (2.4)].

Pediatric Patients: The pharmacokinetics of aliskiren have not been investigated in patients <18 years of age [see Dosage and Administration (2.4)].

Geriatric Patients: Exposure (measured by AUC) is increased in elderly patients ≥65 years. Adjustment of the starting dose is not required in these patients [see Dosage and Administration (2.4)].

Race: The pharmacokinetic differences between Blacks, Caucasians, and the Japanese are minimal.

13 NONCLINICAL TOXICOLOGY

13.1 Carcinogenesis, Mutagenesis, Impairment of Fertility

Carcinogenic potential was assessed in a 2-year rat study and a 6-month transgenic (rasH2) mouse study with aliskiren hemifumarate at oral doses of up to 1500 mg aliskiren/kg/day. Although there were no statistically significant increases in tumor incidence associated with exposure to aliskiren, mucosal epithelial hyperplasia (with or without erosion/ulceration) was observed in the lower gastrointestinal tract at doses of ≥750 mg/kg/day in both species, with a colonic adenoma identified in one rat and a cecal adenocarcinoma identified in another, rare tumors in the strain of rat studied. On a systemic exposure (AUC0-24hr) basis, 1500 mg/kg/day in the rat is about 4 times and in the mouse about 1.5 times the maximum recommended human dose (300 mg aliskiren/day). Mucosal hyperplasia in the cecum or colon of rats was also observed at doses of 250 mg/kg/day (the lowest tested dose) as well as at higher doses in 4- and 13-week studies.

Aliskiren hemifumarate was devoid of genotoxic potential in the Ames reverse mutation assay with S. typhimurium and E. coli, the in vitro Chinese hamster ovary cell chromosomal aberration assay, the in vitro Chinese hamster V79 cell gene mutation test and the in vivo mouse bone marrow micronucleus assay.

Fertility of male and female rats was unaffected at doses of up to 250 mg aliskiren/kg/day (8 times the maximum recommended human dose of 300 mg Tekturna/60 kg on a mg/m^2 basis.)

13.2 Animal Toxicology and/or Pharmacology

Reproductive Toxicology Studies: Reproductive toxicity studies of aliskiren hemifumarate did not reveal any evidence of teratogenicity at oral doses up to 600 mg aliskiren/kg/day (20 times the maximum recommended human dose (MHRD) of 300 mg/day on a mg/m^2 basis) in pregnant rats or up to 100 mg aliskiren/kg/day (7 times the MRHD on a mg/m^2 basis) in pregnant rabbits. Fetal birth weight was adversely affected in rabbits at 50 mg/kg/day (3.2 times the MRHD on a mg/m^2 basis). Aliskiren was present in placenta, amniotic fluid and fetuses of pregnant rabbits.

14 CLINICAL STUDIES

14.1 Aliskiren Monotherapy

The antihypertensive effects of Tekturna have been demonstrated in six randomized, double-blind, placebo-controlled 8-week clinical trials in patients with mild-to-moderate hypertension. The placebo response and placebo-subtracted changes from baseline in seated trough cuff blood pressure are shown in Table 1.

Table 1: Reductions in Seated Trough Cuff Blood Pressure in the Placebo-Controlled Studies
 |  | Aliskiren daily dose, mg
Study | Placebo mean change | 75 | 150 | 300 | 600
 |  | Placebo-subtracted | Placebo-subtracted | Placebo-subtracted | Placebo-subtracted
1 | 2.9/3.3 | 5.7/4* | 5.9/4.5* | 11.2/7.5* | --
2 | 5.3/6.3 | -- | 6.1/2.9* | 10.5/5.4* | 10.4/5.2*
3 | 10/8.6 | 2.2/1.7 | 2.1/1.7 | 5.1/3.7* | --
4 | 7.5/6.9 | 1.9/1.8 | 4.8/2* | 8.3/3.3* | --
5 | 3.8/4.9 | -- | 9.3/5.4* | 10.9/6.2* | 12.1/7.6*
6 | 4.6/4.1 | -- | -- | 8.4/4.9† | --

*p<0.05 vs. placebo by ANCOVA with Dunnett’s procedure for multiple comparisons

†p<0.05 vs. placebo by ANCOVA for the pairwise comparison.

The studies included approximately 2,730 patients given doses of 75-600 mg of aliskiren and 1,231 patients given placebo. As shown in Table 1, there is some increase in response with administered dose in all studies, with reasonable effects seen at 150-300 mg, and no clear further increased at 600 mg. A substantial proportion (85%-90%) of the blood pressure lowering effect was observed within 2 weeks of treatment studies with ambulatory blood pressure monitoring showed reasonable control throughout the interdosing interval; the ratios of mean daytime to mean nighttime ambulatory BP range from 0.6 to 0.9.

Patients in the placebo-controlled trials continued open-label aliskiren for up to one year. A persistent blood pressure lowering effect was demonstrated by a randomized withdrawal study (patients randomized to continue drug or placebo), which showed a statistically significant difference between patients kept on aliskiren and those randomized to placebo. With cessation of treatment, blood pressure gradually returned toward baseline levels over a period of several weeks. There was no evidence of rebound hypertension after abrupt cessation of therapy.

Aliskiren lowered blood pressure in all demographic subgroups, although Black patients tended to have smaller reduction than Caucasians and Asians, as has been seen with ACE inhibitors and ARBs.

There are no studies of Tekturna or members of the direct renin inhibitors demonstrating reductions in cardiovascular risk in patients with hypertension.

14.2 Aliskiren in Combination with Other Antihypertensives

Hydrochlorothiazide

Aliskiren 75, 150, and 300 mg and hydrochlorothiazide 6.25, 12.5, and 25 mg were studied alone and in combination in an 8-week, 2,776-patient, randomized, double-blind, placebo-controlled, parallel-group, 15-arm factorial study. Blood pressure reductions with the combinations were greater than the reductions with the monotherapies as shown in Table 2.

Table 2: Placebo-Subtracted Reductions in Seated Trough Cuff Blood Pressure in Combination with Hydrochlorothiazide
 |  | Hydrochlorothiazide, mg
Aliskiren, mg | Placebo mean change | 0 | 6.25 | 12.5 | 25
 |  | Placebo-subtracted | Placebo-subtracted | Placebo-subtracted | Placebo-subtracted
0 | 7.5/6.9 | -- | 3.5/2.1 | 6.4/3.2 | 6.8/2.4
75 | -- | 1.9/1.8 | 6.8/3.8 | 8.2/4.2 | 9.8/4.5
150 | -- | 4.8/2 | 7.8/3.4 | 10.1/5 | 12/5.7
300 | -- | 8.3/3.3 | -- | 12.3/7 | 13.7/7.3

Valsartan

Aliskiren 150 and 300 mg and valsartan 160 and 320 mg were studied alone and in combination in an 8-week, 1,797-patient, randomized, double-blind, placebo-controlled, parallel-group, 4-arm, dose-escalation study. The dosages of aliskiren and valsartan were started at 150 and 160 mg, respectively, and increased at four weeks to 300 mg and 320 mg, respectively. Seated trough cuff blood pressure was measured at baseline, 4, and 8 weeks. Blood pressure reductions with the combinations were greater than the reductions with the monotherapies as shown in Table 3.

Table 3: Placebo-Subtracted Reductions in Seated Trough Cuff Blood Pressure in Combination with Valsartan
Aliskiren, mg | Placebo mean change | Valsartan, mg
 |  | 0 | 160 | 320
0 | 4.6/4.1* | -- | 5.6/3.9 | 8.2/5.6
150 | -- | 5.4/2.7 | 10.0/5.7 | --
300 | -- | 8.4/4.9 | -- | 12.6/8.1

* The placebo change is 5.2/4.8 for week 4 endpoint which was used for the dose groups containing Aliskiren 150 mg or Valsartan 160 mg.

Amlodipine

Aliskiren 150 mg and 300 mg and amlodipine besylate 5 mg and 10 mg were studied alone and in combination in an 8-week, 1,685-patient, randomized, double-blind, placebo-controlled, multifactorial study. Treatment with aliskiren and amlodipine resulted overall in significantly greater reductions in diastolic and systolic blood pressure compared to the respective monotherapy components as shown in Table 4.

Table 4: Placebo-Subtracted Reductions in Seated Trough Cuff Blood Pressure in Combination with Amlodipine
Aliskiren, mg | Placebo mean change | Amlodipine, mg
 |  | 0 | 5 | 10
0 | 5.4/6.8* | -- | 5.6/9.0 | 8.5/14.3
150 | -- | 2.6/3.9 | 8.6/13.9 | 10.8/17.1
300 | -- | 4.9/8.6 | 9.6/15.0 | 11.1/16.4

ACE inhibitors

Aliskiren has not been studied when added to maximal doses of ACE inhibitors to determine whether aliskiren produces additional blood pressure reduction.

16 HOW SUPPLIED/STORAGE AND HANDLING

Tekturna is supplied as a light-pink, biconvex round tablet containing 150 mg of aliskiren, and as a light-red biconvex ovaloid tablet containing 300 mg of aliskiren. Tablets are imprinted with NVR on one side and IL, IU, on the other side of the 150, and 300 mg tablets, respectively.

All strengths are packaged in bottles and unit-dose blister packages (10 strips or 10 tablets) as described below in Table 5.

Table 5: Tekturna Tablets Supply
Tablet | Color | Imprint | Imprint
 |  | Side 1 | Side 2 | Bottle of 30
150 mg | Light-Pink | NVR | IL | 54868-5772-0
300 mg | Light-Red | NVR | IU | 54868-6042-0

Store at 25ºC (77ºF); excursions permitted to 15-30ºC (59-86ºF) [See USP Controlled Room Temperature]. Protect from moisture.

Dispense in original container.

17 PATIENT COUNSELING INFORMATION

See FDA-approved patient labeling (Patient Information)

Information for Patients

Pregnancy: Female patients of child bearing age should be told about the consequences of exposure to drugs that act on the renin-angiotensin system. Discuss other treatment options with female patients planning to become pregnant. Patients should be asked to report pregnancies to their physicians as soon as possible.

Angioedema: Angioedema, including laryngeal edema, may occur at any time during treatment with Tekturna. Patients should be advised and told to report immediately any signs or symptoms suggesting angioedema (swelling of face, extremities, eyes, lips, tongue, difficulty in swallowing or breathing) and to take no more drug until they have consulted with the prescribing physicians.

Symptomatic Hypotension: A patient receiving Tekturna should be cautioned that lightheadedness can occur, especially during the first days of therapy, and that it should be reported to the prescribing physician. The patients should be told that if syncope occurs, Tekturna should be discontinued until the physician has been consulted.

All patients should be cautioned that inadequate fluid intake, excessive perspiration, diarrhea, or vomiting can lead to an excessive fall in blood pressure, with the same consequences of lightheadedness and possible syncope.

Potassium Supplements: A patient receiving Tekturna should be told not to use potassium supplements or salt substitutes containing potassium without consulting the prescribing physician.

Relationship to Meals: Patients should establish a routine pattern for taking Tekturna with regard to meals. High-fat meals decrease absorption substantially.

T2011-116

FDA approved patient labeling

PATIENT INFORMATION

Tekturna (pronounced tek-turn-a)

(aliskiren)

Tablets

Dosing Strengths:

150 mg tablets

300 mg tablets

Available by Prescription Only

Read the patient information that comes with Tekturna before you start taking it and each time you get a refill. There may be new information. This leaflet does not replace talking to your doctor about your condition or treatment. If you have any questions about Tekturna, ask your doctor or pharmacist.

IMPORTANT WARNING: If you get pregnant, stop taking Tekturna and call your doctor right away. Tekturna may harm an unborn baby, causing injury and even death. If you plan to become pregnant, talk to your doctor about other treatment options before taking Tekturna.

What Is Tekturna?

Tekturna can help your blood vessels relax and widen so blood pressure is lower. Tekturna is a type of prescription medicine called a direct renin inhibitor. By reducing renin, it helps to reduce blood pressure.

What Is High Blood Pressure (Hypertension)?

Blood pressure is the force that pushes the blood through your blood vessels to all the organs of your body. You have high blood pressure when the force of your blood moving through your blood vessels is too great. Renin (pronounced REE-nin) is a chemical in the body that starts a process that makes blood vessels narrow, leading to high blood pressure. Drugs that lower blood pressure lower your risk of having a stroke or heart attack.

High blood pressure makes the heart work harder to pump blood throughout the body and causes damage to the blood vessels. If high blood pressure is not treated, it can lead to stroke, heart attack, heart failure, kidney failure, and vision problems.

Who Should Not Take Tekturna?

- If you get pregnant, stop taking Tekturna and call your doctor right away. If you plan to become pregnant, talk to your doctor about other treatment options for your high blood pressure.
- Do not take Tekturna if you are allergic to any of its ingredients. See the end of this leaflet for a complete list of the ingredients in Tekturna.
- Tekturna has not been studied in children under 18 years of age.

What Should I Tell My Doctor Before Taking Tekturna?

Tell your doctor about all your medical conditions, including whether you:

- are pregnant or planning to become pregnant, see IMPORTANT WARNING
- are breast-feeding. It is not known if Tekturna passes into your breast milk. You should choose either to take Tekturna or breast-feed, but not both.
- have kidney problems.
- are allergic to any of the ingredients in Tekturna, see “what are the ingredients in Tekturna”
- have ever had a reaction called angioedema, to an ACE inhibitor medicine. Angioedema causes swelling of the face, lips, tongue, throat, arms, and legs, and may cause difficulty breathing.

Tell your doctor about all the medicines you take including prescription and nonprescription medicines, vitamins and herbal supplements. Especially tell your doctor if you are taking:

- other medicines for high blood pressure or a heart problem.
- Atorvastatin (medicine to lower cholesterol in your blood).
- water pills (also called “diuretics”).
- medicines for treating fungus or fungal infections.
- cyclosporine (a medicine used to suppress the immune system).
- potassium-containing medicines, potassium supplements, or salt substitutes containing potassium.

Your doctor or pharmacist will know what medicines are safe to take together.

How Should I Take Tekturna?

- Take Tekturna once a day, at the same time each day. As with any blood pressure medication, it is important to take Tekturna on a regular daily basis exactly as prescribed by your doctor.
- Tekturna can be taken by itself or safely in combination with other medicines to lower high blood pressure. Your doctor may change your dose if needed.
- Tekturna can be taken with or without food.
- If you miss a dose, take it as soon as you remember. If it is close to your next dose, do not take the missed dose. Just take the next dose at your regular time.
- If you take too much Tekturna, call your doctor or Poison Control Center, or go to the nearest hospital emergency room.

What Are Possible Side Effects Of Tekturna?

Tekturna may cause serious side effects:

- Injury or death to an unborn baby. See IMPORTANT WARNING.
- Low blood pressure (hypotension). Your blood pressure may get too low if you also take water pills, are on a low-salt diet, get dialysis treatments, have heart problems, or get sick with vomiting or diarrhea. Lie down if you feel faint or dizzy. Call your doctor right away.
- Angioedema: Aliskiren can cause swelling of the face, lips, tongue, throat, arms and legs or the whole body. Get medical help right away and tell your doctor if you get any one or more of these symptoms. Angioedema can happen at any time while you are taking Tekturna.

Common side effects of Tekturna include:

diarrhea

cough

dizziness

headache

flu-like symptoms

back pain

tiredness

Less common side effects include rash.

Tell your doctor if you have any side effect that bothers you or that does not go away. These are not all of the possible side effects of Tekturna. For a complete list of side effects, ask your doctor or pharmacist.

How Do I Store Tekturna?

- Store Tekturna tablets at room temperature between 59o to 86oF (15°-30°C).
- Keep Tekturna in the original prescription bottle in a dry place. Do not remove the desiccant (drying agent) from the bottle.
- Keep Tekturna and all medicines out of the reach of children.

General Information About Tekturna

Medicines are sometimes prescribed for conditions not listed in the patient information leaflet. Do not take Tekturna for a condition for which it was not prescribed. Do not give Tekturna to other people, even if they have the same condition or symptoms you have. It may harm them.

This leaflet summarizes the most important information about Tekturna. If you have more questions about Tekturna talk with your doctor. You can ask your doctor or pharmacist for information that is written for healthcare professionals.

For more information about Tekturna, ask your doctor or pharmacist, visit www.Tekturna.com, or call 1-888-Tekturna (1-888-835-8876).

What are the ingredients in Tekturna?

Active Ingredients: Aliskiren (Tekturna)

Inactive Ingredients: colloidal silicone dioxide, crospovidone, hypromellose, iron oxide colorants, magnesium stearate, microcrystalline cellulose, polyethylene glycol, talc, and titanium dioxide.

Manufactured by:

Novartis Pharma AG, Stein, Switzerland

Novartis Pharma Produktions GmbH, Wehr, Germany

Distributed by:

Novartis Pharmaceuticals Corporation

East Hanover, NJ 07936

© Novartis

T2011-116/T2009-52

October 2011/November 2009

Additional barcode labeling by:
Physicians Total Care, Inc.
Tulsa, Oklahoma 74146

PACKAGE LABEL

PRINCIPAL DISPLAY PANEL

Package Label – 150 mg

Rx Only NDC 54868-5772-0

Tekturna® (aliskiren) Tablets

150 mg

30 tablets

PACKAGE LABEL

PRINCIPAL DISPLAY PANEL

Package Label – 300 mg

Rx Only NDC 54868-6042-0

Tekturna® (aliskiren) Tablets

300 mg

30 tablets